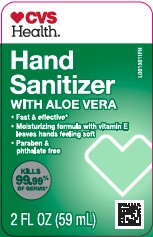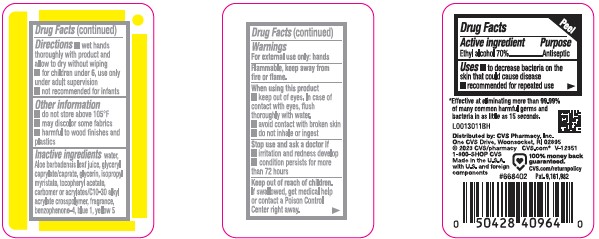 DRUG LABEL: Advanced Hand Sanitizer
NDC: 59779-070 | Form: GEL
Manufacturer: CVS Pharmacy, Inc.
Category: otc | Type: HUMAN OTC DRUG LABEL
Date: 20260203

ACTIVE INGREDIENTS: ALCOHOL 70 mL/100 mL
INACTIVE INGREDIENTS: WATER; ALOE VERA LEAF; GLYCERYL CAPRYLATE/CAPRATE; GLYCERIN; ISOPROPYL MYRISTATE; .ALPHA.-TOCOPHEROL ACETATE; CARBOMER HOMOPOLYMER, UNSPECIFIED TYPE; ACRYLATES/C10-30 ALKYL ACRYLATE CROSSPOLYMER (60000 MPA.S); SULISOBENZONE; FD&C BLUE NO. 1; FD&C YELLOW NO. 5

CVS 439.001/439AC
Advanced Hand Sanitizer with Aloe

Active ingredient

Ethyl alcohol 70%

Purpose

Antiseptic

Uses

- to decrease bacteria on the skin that could cause disease
- recommended for repeated use

Warnings

For external use only-hands

Flammable, keep away from fire or flame.

When using this product

- keep out of eyes. In case of contact with eyes, flush thoroughly with water.
- avoid contact with broken skin
- do not inhale or ingest

Stop use and ask a doctor if

- irritation and redness develop
- condition persists for more than 72 hours

Keep out of reach of children.

If swallowed, get medical help or contact a Poison Control Center right away.

Directions

- wet hands thoroughly with product and allow to dry without wiping
- for children under 6, use only under adult supervision
- not recommended for infants

Other information

- do not store above 105⁰ F
- may discolor some fabrics
- harmful to wood finishes and plastics

Inactive ingredients

water, Aloe barbadensis leaf juice, glyceryl caprylate/caprate, glycerin, isopropyl myristate, tocopheryl acetate, carbomer or acrylates/C10-30 alkyl acrylate crosspolymer, fragrance, benzophenone-4, blue 1, yellow 5

Claim

*Effective at eliminating more than 99.99% of many common harmful germs and bacteria in as little as 15 seconds.

Adverse reaction

Distributed by: CVS Pharmacy, Inc.

One CVS Drive, Woonsocket, RI 02895

©2023 CVS/Pharmacy

CVS.com 1-800-SHOP CVS

Made in the U.S.A. with U.S. and foreign components

100% money back guaranteed.

CVS.com/returnpolicy

Principal display panel

CVS Health®

Hand Sanitizer

WITH ALOE VERA

- Fast & effective*
- Moisturizing formula with vitamin E leaves hands feeling soft
- Paraben & phthalate free

KILLS 99.99% OF GERMS*

2 FL OZ (59 mL)